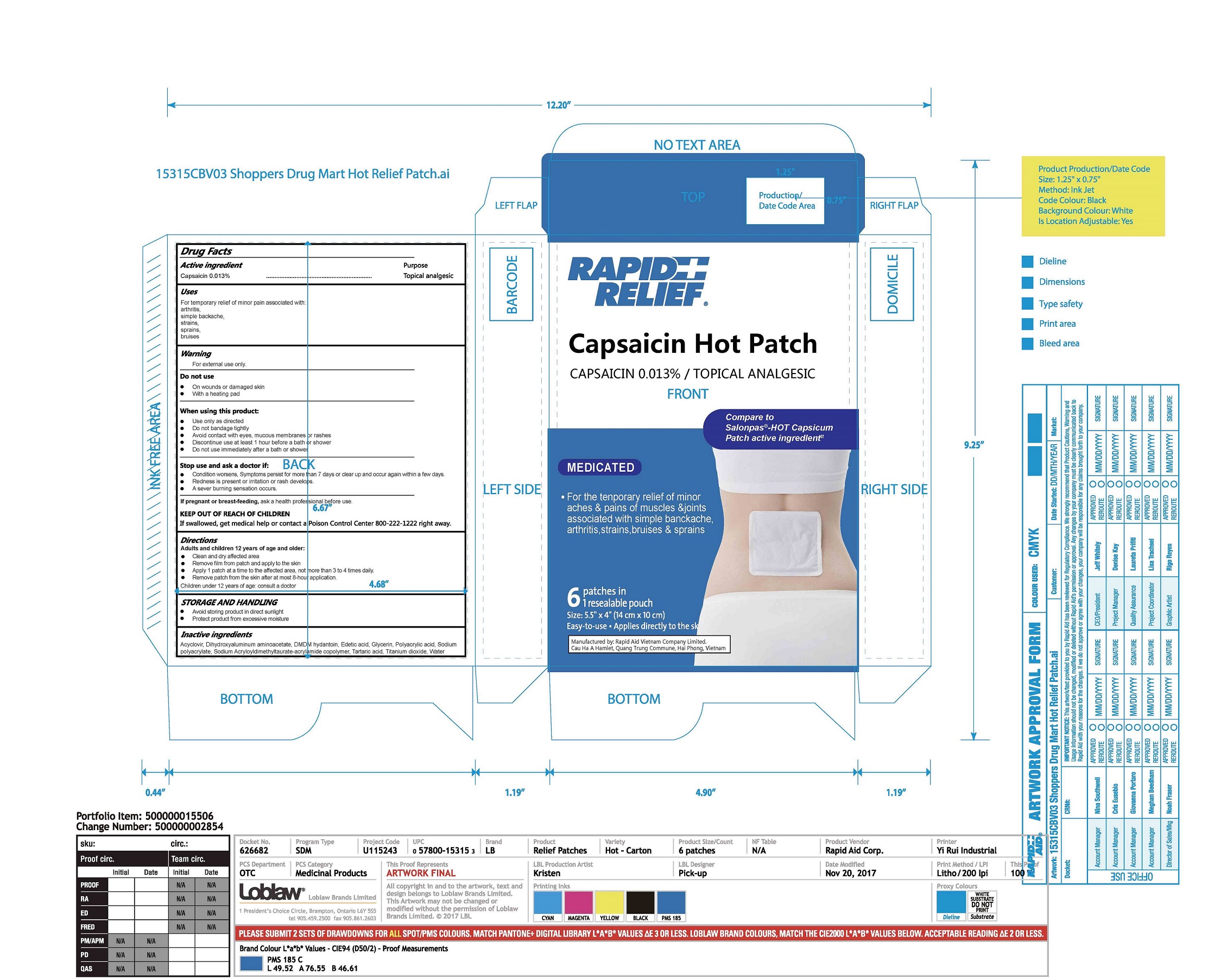 DRUG LABEL: Rapid Relief Hot Relief Patch
NDC: 83569-005 | Form: PATCH
Manufacturer: RAPID AID VIET NAM CO., LTD
Category: otc | Type: HUMAN OTC DRUG LABEL
Date: 20251016

ACTIVE INGREDIENTS: CAPSAICIN 0.013 g/100 g
INACTIVE INGREDIENTS: ACYCLOVIR; POLYACRYLIC ACID (300000 MW); POLYACRYLIC ACID (800000 MW); DIHYDROXYALUMINUM AMINOACETATE; GLYCERIN; WATER; DMDM HYDANTOIN; EDETATE DISODIUM ANHYDROUS; SODIUM POLYACRYLATE (8000 MW); SODIUM ACRYLOYLDIMETHYLTAURATE-ACRYLAMIDE COPOLYMER (1:1; 90000-150000 MPA.S); TARTARIC ACID; TITANIUM DIOXIDE

Active Ingredient(s)

Capsaicin 0.013 %

Purpose

Topical analgesic

Use

For temporary relief of minor pain associated with:
arthritis,
simple backache,
strains,
sprains,
bruises

Warnings

For external use only.

Do not use

On wounds or damaged skin
With a heating pad

When using this product:

 Use only as directed
 Do not bandage tightly
 Avoid contact with eyes, mucous membranes or rashes
 Discontinue use at least 1 hour before a bath or shower
 Do not use immediately after a bath or shower

Stop use and ask a doctor if:

 Condition worsens, Symptoms persist for more than 7 days or clear up and occur again within a few days.
 Redness is present or irritation or rash develops.
 A sever burning sensation occurs.

KEEP OUT OF REACH OF CHILDREN

If swallowed, get medical help or contact a Poison Control Center right away.

If pregnant or breast feeding

ask a health professional before use.

Directions

Adults and children 12 years of age and older:
 Clean and dry affected area
 Remove film from patch and apply to the skin
 Apply 1 patch at a time to the affected area, not more than 3 to 4 times daily.
 Remove patch from the skin after at most 8-hour application.
Children under 12 years of age: consult a doctor

STORAGE AND HANDLING

 Avoid storing product in direct sunlight
 Protect product from excessive moisture

Inactive ingredients

Acyclovir, Dihydroxyaluminum aminoacetetel, DMDM hydantoin, Edetate Disodium Anhydrous, Glycerin, Polyacrylic acid, Sodium polyacrylate, Sodium Acryloyldimethyltaurate-acrylamide copolymer, Tartaric acid, Titanium dioxide, Water